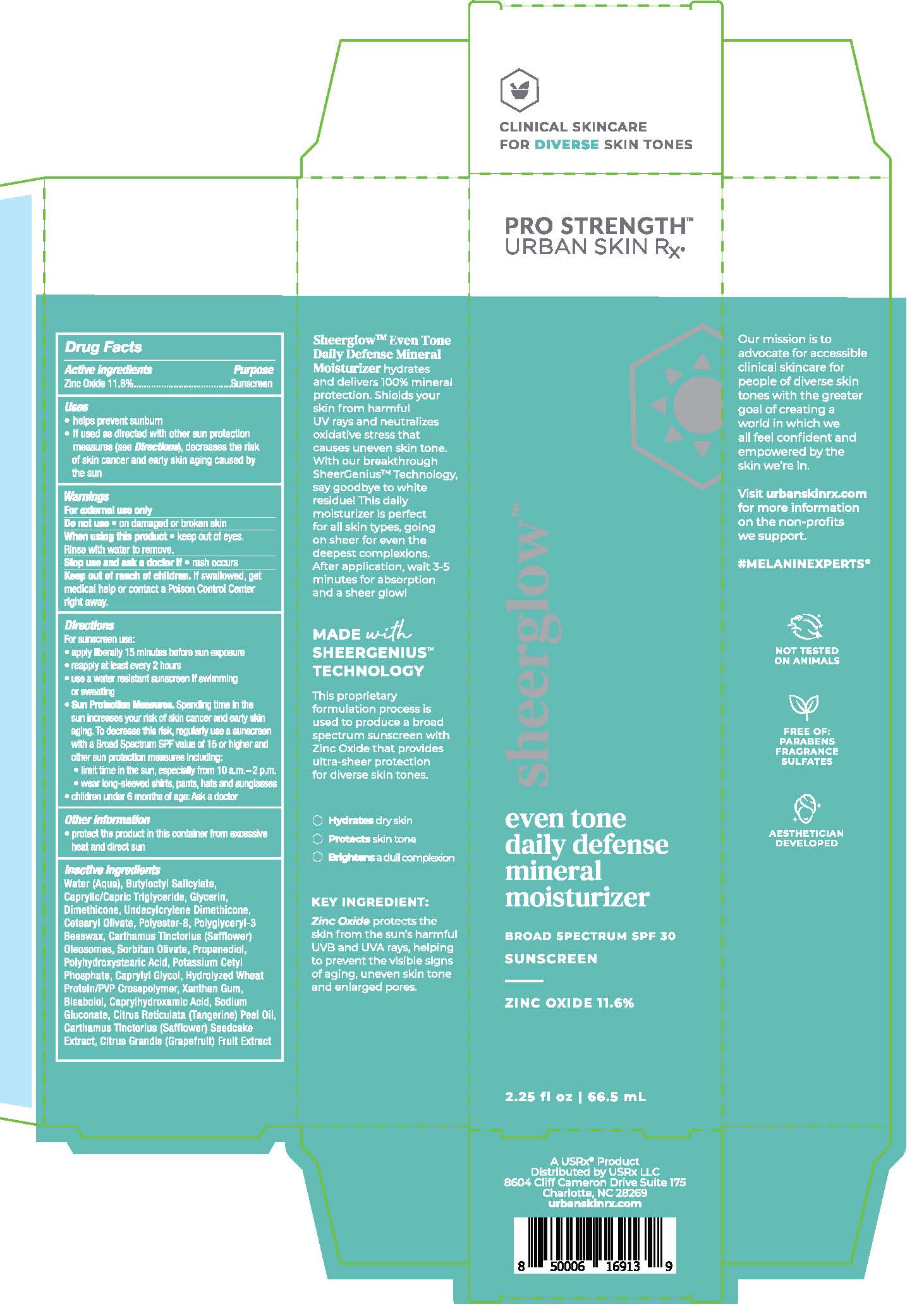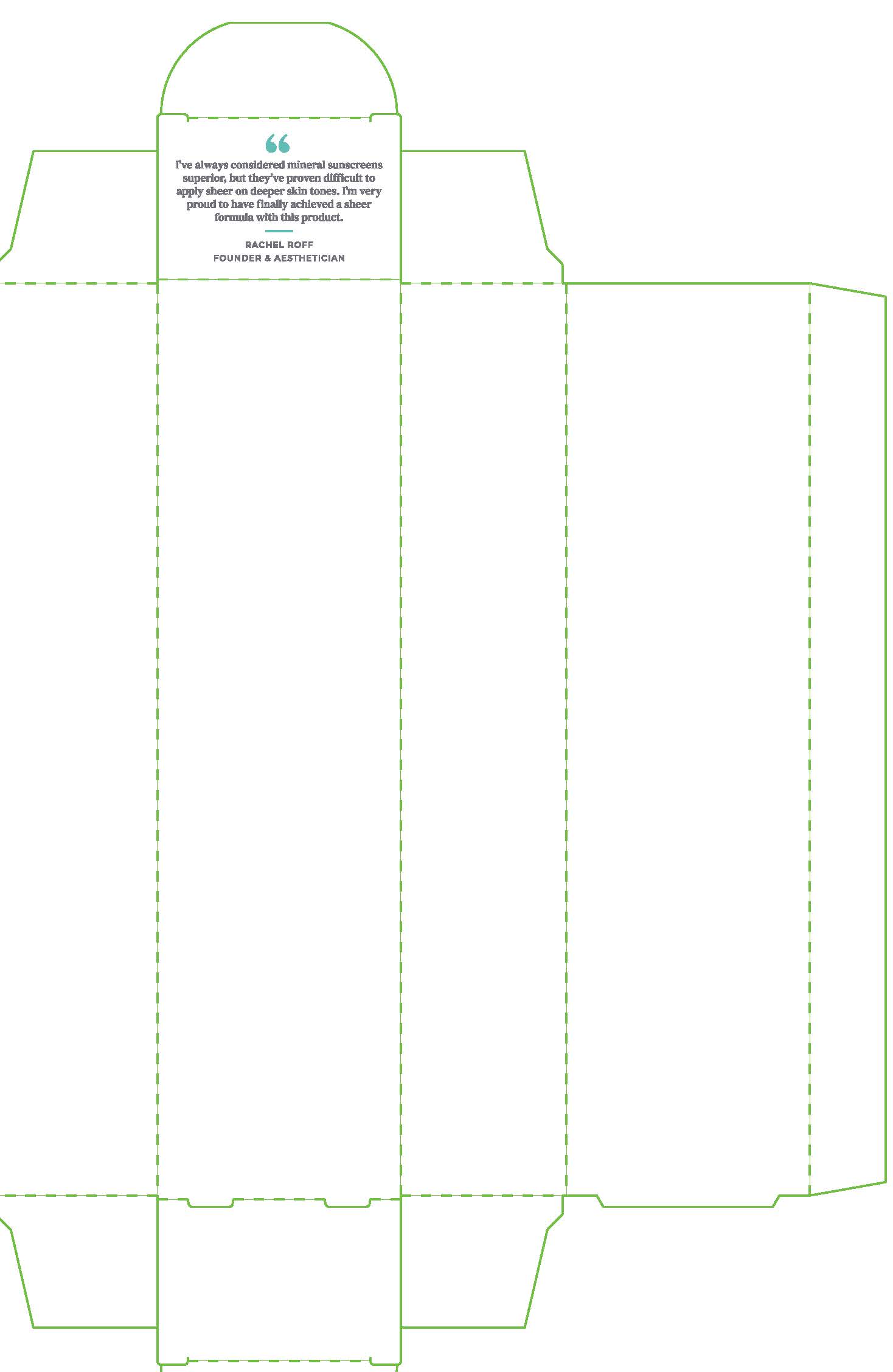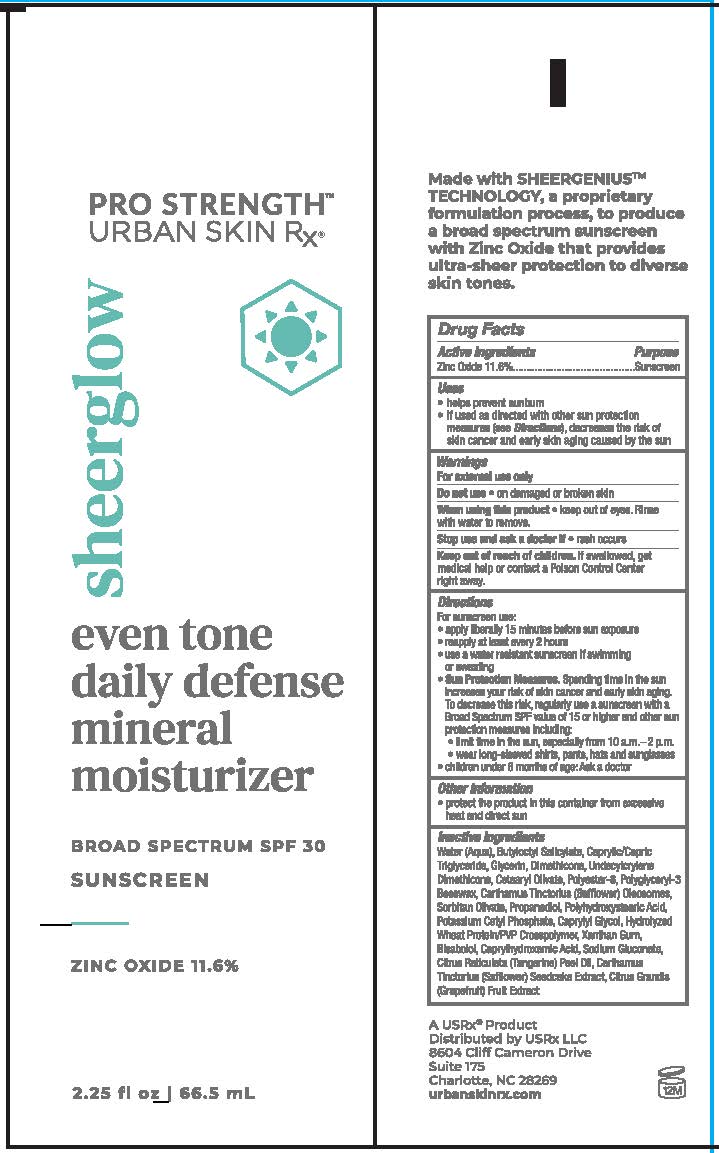 DRUG LABEL: Sheer Glow
NDC: 70809-1910 | Form: CREAM
Manufacturer: USRX LLC
Category: otc | Type: HUMAN OTC DRUG LABEL
Date: 20241001

ACTIVE INGREDIENTS: ZINC OXIDE 11.6 mg/100 mL
INACTIVE INGREDIENTS: PUMMELO; MANDARIN OIL; CARTHAMUS TINCTORIUS (SAFFLOWER) OLEOSOMES; METHYL DIHYDROABIETATE; BUTYLOCTYL SALICYLATE; CAPRYLHYDROXAMIC ACID; PROPANEDIOL; XANTHAN GUM; POLYESTER-8 (1400 MW, CYANODIPHENYLPROPENOYL CAPPED); LEVOMENOL; SODIUM GLUCONATE; UNDECYLCRYLENE DIMETHICONE (10000 MW); WATER; POTASSIUM CETYL PHOSPHATE; DIMETHICONE; GLYCERIN; CAPRYLYL GLYCOL; POLYHYDROXYSTEARIC ACID (2300 MW); HYDROLYZED WHEAT PROTEIN (ENZYMATIC, 3000 MW); CARTHAMUS TINCTORIUS SEEDCAKE; CETEARYL OLIVATE; SORBITAN OLIVATE; MEDIUM-CHAIN TRIGLYCERIDES

70809-1910 Sheer Glow

Active Ingredients:

Zinc Oxide 11.6%

Purpose

Sunscreen

Use(s):

Helps prevent sunburn.

If used as directed with other sun protection measures (see directions), decreases the risk of skin canger and early skin aging caused by the sun.

Warnings:

For External use only.

Do not use

on damaged or broken skin.

When using this product,

keep out of eyes. Rinse with water to remove.

Stop use and ask a doctor

if rash occurs.

Keep out of reach of children.

If product is swallowed, get medical help or contact a Poison Control Center right away.

Directions:

For Sunscreen use:

- Apply liberally and evenly 15 minutes before sun exposure
- Reapply at least every 2 hours
- Use a water resistant sunscreen if swimming or sweating

Sun Protection Measures.

Spending time in the sun increases your risk of skin cancer and early skin aging. To decrease this risk, regularly use a sunscreen with a Broad Spectrum SPF value of 15 or higher and other sun protection measures including:

- Limit time in the sun, especially from 10 a.m. to 2 p.m.
- Wear long-sleeved shirts, pants, hats and sunglasses
- Children under 6 months: ask a doctor

INACTIVE INGREDIENTS:

Water (Aqua), Butyloctyl Salicylate, Caprylic/Capric Triglyceride, Glycerin, Dimethicone, Undecylcrylene Dimethicone, Cetearyl Olivate, Polyester-8, Polyglyceryl-3 Beeswax, Carthamus Tinctorius (Safflower) Oleosomes, Sorbitan Olivate, Propanediol, Polyhydroxystearic Acid, Potassium Cetyl Phosphate, Caprylyl Glycol, Hydrolyzed Wheat Protein/PVP Crosspolymer, Xanthan Gum, Bisabolol, Caprylhydroxamic Acid, Sodium Gluconate, Citrus Reticulata (Tangerine) Peel Oil, Carthamus Tinctorius (Safflower) Seedcake Extract, Citrus Grandis (Grapefruit) Fruit Extract.

Other Information:

Protect the product in this container from excessive heat and direct sun.